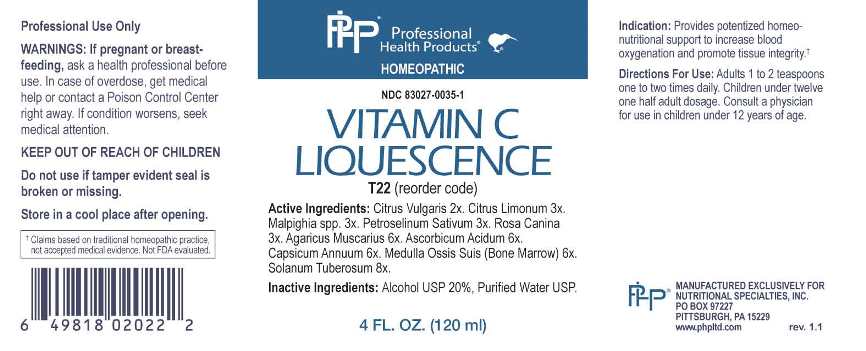 DRUG LABEL: Vitamin C Liquescence
NDC: 83027-0035 | Form: LIQUID
Manufacturer: Nutritional Specialties, Inc.
Category: homeopathic | Type: HUMAN OTC DRUG LABEL
Date: 20230328

ACTIVE INGREDIENTS: CITRUS AURANTIUM FRUIT RIND 2 [hp_X]/1 mL; LEMON JUICE 3 [hp_X]/1 mL; ACEROLA 3 [hp_X]/1 mL; PETROSELINUM CRISPUM WHOLE 3 [hp_X]/1 mL; ROSA CANINA FRUIT 3 [hp_X]/1 mL; AMANITA MUSCARIA FRUITING BODY 6 [hp_X]/1 mL; ASCORBIC ACID 6 [hp_X]/1 mL; CAPSICUM 6 meq/1 mL; SUS SCROFA BONE MARROW 6 [hp_X]/1 mL; SOLANUM TUBEROSUM WHOLE 8 [hp_X]/1 mL
INACTIVE INGREDIENTS: WATER; ALCOHOL

DRUG FACTS:

ACTIVE INGREDIENTS:

Citrus Vulgaris 2X, Citrus Limonum 3X, Malpighia Spp 3X, Petroselinum Sativum 3X, Rosa Canina 3X, Agaricus Muscarius 6X, Ascorbicum Acidum 6X, Capsicum Annuum 6X, Medulla Ossis Suis (Bone Marrow) 6X, Solanum Tuberosum 8X.

PURPOSE:

Provides potentized homeo-nutritional support to increase blood oxygenation and promote tissue integrity.†

†Claims based on traditional homeopathic practice, not accepted medical evidence. Not FDA evaluated.

WARNINGS:

Professional Use Only

If pregnant or breast-feeding, ask a health professional before use.

In case of overdose, get medical help or contact a Poison Control Center right away.

If condition worsens, seek medical attention.

KEEP OUT OF REACH OF CHILDREN

Do not use if tamper evident seal is broken or missing.

Store in a cool place after opening

KEEP OUT OF REACH OF CHILDREN:

In case of overdose, get medical help or contact a Poison Control Center right away.

DIRECTIONS:

Adults 1 to 2 teaspoons one to two times daily. Children under twelve one half adult dosage. Consult a physician for use in children under 12 years of age.

INDICATIONS:

Provides potentized homeo-nutritional support to increase blood oxygenation and promote tissue integrity.†

†Claims based on traditional homeopathic practice, not accepted medical evidence. Not FDA evaluated.

INACTIVE INGREDIENTS:

Alcohol USP 20%, Purified Water USP.

QUESTIONS:

MANUFACTURED EXCLUSIVELY FOR

NUTRITIONAL SPECIALTIES, INC.

PO BOX 97227

PITTSBURG, PA 15229

www.phpltd.com

PACKAGE LABEL DISPLAY:

Professional

Health Products

HOMEOPATHIC

NDC 83027-0035-1

VITAMIN C

LIQUESCENCE

4 FL. OZ (120 ml)